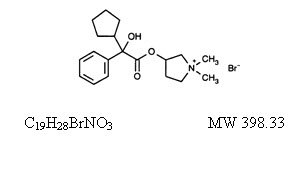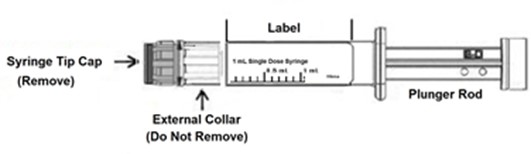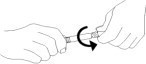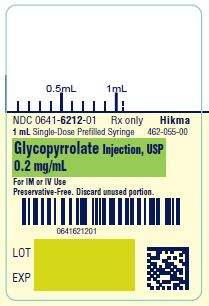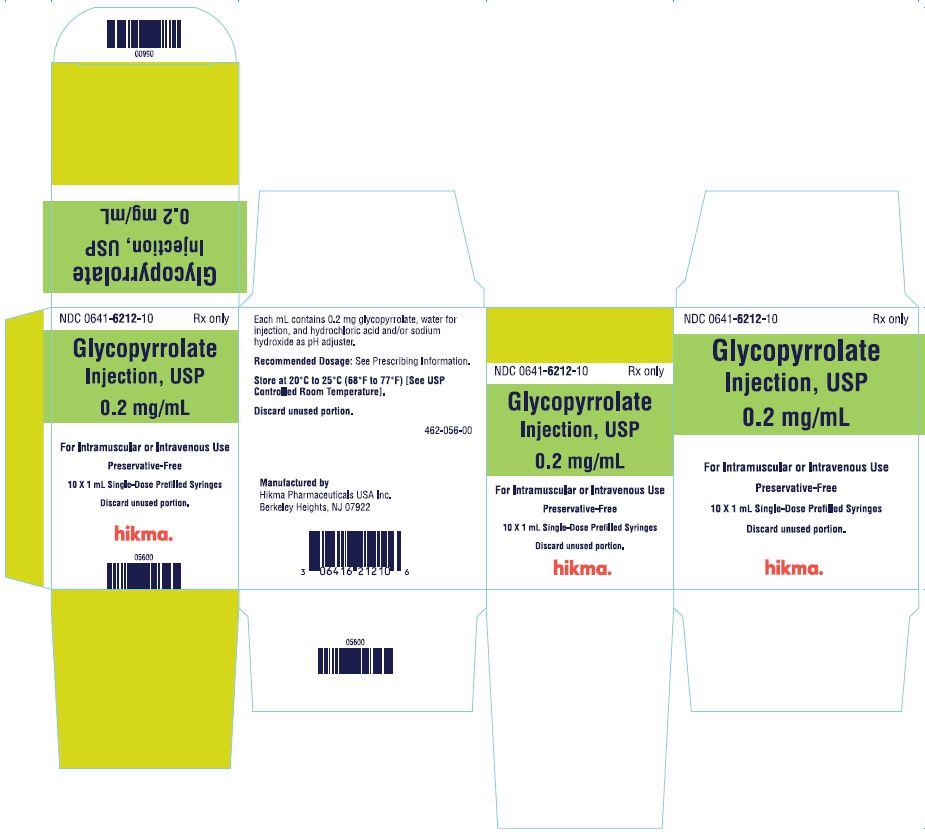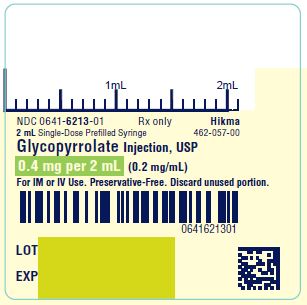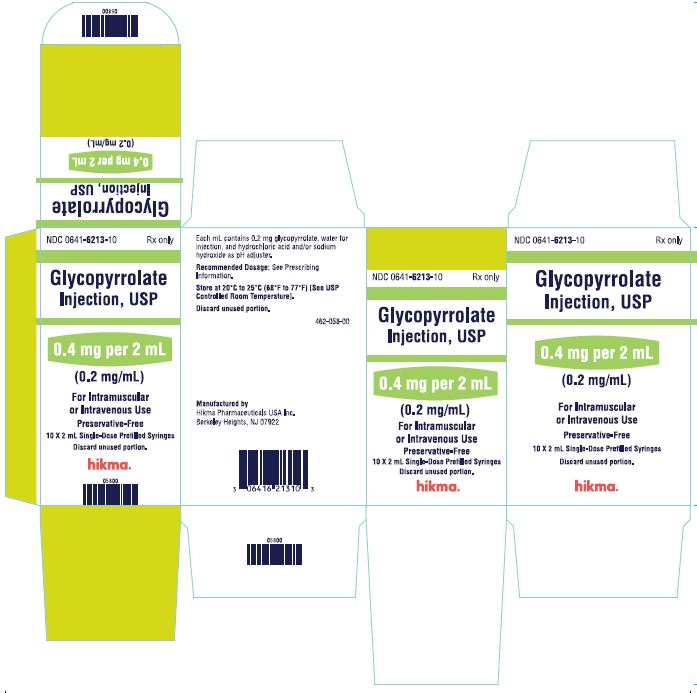 DRUG LABEL: Glycopyrrolate
NDC: 0641-6212 | Form: INJECTION
Manufacturer: Hikma Pharmaceuticals USA Inc.
Category: prescription | Type: HUMAN PRESCRIPTION DRUG LABEL
Date: 20251009

ACTIVE INGREDIENTS: GLYCOPYRROLATE 0.2 mg/1 mL
INACTIVE INGREDIENTS: WATER; HYDROCHLORIC ACID; SODIUM HYDROXIDE

Glycopyrrolate Injection, USP

Rx only

DESCRIPTION

Glycopyrrolate Injection, USP is a synthetic anticholinergic agent. Each 1 mL contains:

Glycopyrrolate, USP 0.2 mg
Water for Injection, USP q.s.

pH adjusted, when necessary, with hydrochloric acid and/or sodium hydroxide.

For Intramuscular (IM) or Intravenous (IV) administration. Solution does not contain preservatives.

Glycopyrrolate is a quaternary ammonium salt with the following chemical name:
3[(cyclopentylhydroxyphenylacetyl)oxy]-1,1-dimethyl pyrrolidinium bromide. The molecular formula is C19H28BrNO3 and the molecular weight is 398.33.

Its structural formula is as follows:

Glycopyrrolate occurs as a white, odorless crystalline powder. It is soluble in water and alcohol, and practically insoluble in chloroform and ether.

Unlike atropine, glycopyrrolate is completely ionized at physiological pH values. Glycopyrrolate Injection, USP, is a clear, colorless, sterile liquid; pH 2.0 to 3.0. The partition coefficient of glycopyrrolate in a n-octanol/water system is 0.304 (log10 P= -1.52) at ambient room temperature (24°C).

CLINICAL PHARMACOLOGY

Glycopyrrolate, like other anticholinergic (antimuscarinic) agents, inhibits the action of acetylcholine on structures innervated by postganglionic cholinergic nerves and on smooth muscles that respond to acetylcholine but lack cholinergic innervation. These peripheral cholinergic receptors are present in the autonomic effector cells of smooth muscle, cardiac muscle, the sinoatrial node, the atrioventricular node, exocrine glands and, to a limited degree, in the autonomic ganglia. Thus, it diminishes the volume and free acidity of gastric secretions and controls excessive pharyngeal, tracheal, and bronchial secretions.

Glycopyrrolate antagonizes muscarinic symptoms (e.g., bronchorrhea, bronchospasm, bradycardia, and intestinal hypermotility) induced by cholinergic drugs such as the anticholinesterases.

The highly polar quaternary ammonium group of glycopyrrolate limits its passage across lipid membranes, such as the blood-brain barrier, in contrast to atropine sulfate and scopolamine hydrobromide, which are highly non-polar tertiary amines which penetrate lipid barriers easily.

With intravenous injection, the onset of action is generally evident within one minute. Following intramuscular administration, the onset of action is noted in 15 to 30 minutes, with peak effects occurring within approximately 30 to 45 minutes. The vagal blocking effects persist for 2 to 3 hours and the antisialagogue effects persist up to 7 hours, periods longer than for atropine.

Pharmacokinetics

The following pharmacokinetic information and conclusions were obtained from published studies that used nonspecific assay methods.

DISTRIBUTION

The mean volume of distribution of glycopyrrolate was estimated to be 0.42 ± 0.22 L/kg.

METABOLISM

The in vivo metabolism of glycopyrrolate in humans has not been studied.

EXCRETION

The mean clearance and mean T1/2 values were reported to be 0.54 ± 0.14 L/kg/hr and 0.83 ± 0.13 hr, respectively post IV administration. After IV administration of a 0.2 mg radiolabeled glycopyrrolate, 85% of dose recovered was recovered in urine 48 hours postdose and some of the radioactivity was also recovered in bile. After IM administration of glycopyrrolate to adults, the mean T1/2 value is reported to be between 0.55 to 1.25 hrs. Over 80% of IM dose administered was recovered in urine and the bile as unchanged drug and half the IM dose is excreted within 3 hrs. The following table summarizes the mean and standard deviation of pharmacokinetic parameters from a study.

Group | t1/2; (hr) | Vss; (L/kg) | CL; (L/kg/hr) | Tmax; (min) | Cmax; (mcg/L) | AUC; (mcg/L•hr)
(6 mcg/kg IV) | 0.83 ± 0.27 | 0.42 ± 0.22 | 0.54 ± 0.14 | - | - | 8.64 ± 1.49*
(8 mcg/kg IM) | - | - | - | 27.48 ± 6.12 | 3.47 ± 1.48 | 6.64 ± 2.33*

* 0 to 8 hr

SPECIAL POPULATIONS

Gender

Gender differences in pharmacokinetics of glycopyrrolate have not been investigated.

Renal Impairment

In one study glycopyrrolate was administered IV in uremic patients undergoing renal transplantation. The mean elimination half-life was significantly longer (46.8 minutes) than in healthy patients (18.6 minutes). The mean area-under-the-concentration-time curve (10.6 hr-mcg/L), mean plasma clearance (0.43 L/hr/kg), and mean 3-hour urine excretion (0.7%) for glycopyrrolate were also significantly different than those of controls (3.73 hr-mcg/L, 1.14 L/hr/kg, and 50%, respectively). These results suggest that the elimination of glycopyrrolate is severely impaired in patients with renal failure.

Hepatic Impairment

Pharmacokinetic information in patients with hepatic impairment is unavailable.

Pediatrics

Following IV administration (5 mcg/kg glycopyrrolate) to infants and children, the mean T1/2 values were reported to be between 21.6 and 130.0 minutes and between 19.2 and 99.2 minutes, respectively.

INDICATIONS AND USAGE

In Anesthesia

Glycopyrrolate Injection is indicated for use as a preoperative antimuscarinic to reduce salivary, tracheobronchial, and pharyngeal secretions; to reduce the volume and free acidity of gastric secretions; and to block cardiac vagal inhibitory reflexes during induction of anesthesia and intubation. When indicated, Glycopyrrolate Injection may be used intraoperatively to counteract surgically or drug-induced or vagal reflexes associated arrhythmias. Glycopyrrolate protects against the peripheral muscarinic effects (e.g., bradycardia and excessive secretions) of cholinergic agents such as neostigmine and pyridostigmine given to reverse the neuromuscular blockade due to non-depolarizing muscle relaxants.

In Peptic Ulcer

For use in adults to reduce symptoms of a peptic ulcer and as an adjunct to treatment of peptic ulcer when rapid anticholinergic effect is desired or when oral medication is not tolerated.

- Limitations of Use

Robinul Injection is not indicated as monotherapy for the treatment of peptic ulcer because effectiveness in peptic ulcer healing has not been established.

CONTRAINDICATIONS

Known hypersensitivity to glycopyrrolate or any of its inactive ingredients.

In addition, in the management of peptic ulcer patients, because of the longer duration of therapy, Glycopyrrolate Injection may be contraindicated in patients with the following concurrent conditions: glaucoma; obstructive uropathy (for example, bladder neck obstruction due to prostatic hypertrophy); obstructive disease of the gastrointestinal tract (as in achalasia, pyloroduodenal stenosis, etc.); paralytic ileus, intestinal atony of the elderly or debilitated patient; unstable cardiovascular status in acute hemorrhage; severe ulcerative colitis; toxic megacolon complicating ulcerative colitis; myasthenia gravis.

WARNINGS

This drug should be used with great caution, if at all, in patients with glaucoma.

Glycopyrrolate Injection may produce drowsiness or blurred vision. The patient should be cautioned regarding activities requiring mental alertness such as operating a motor vehicle or other machinery or performing hazardous work while taking this drug.

In addition, in the presence of fever, high environmental temperature and/or during physical exercise, heat prostration can occur with use of anticholinergic agents including glycopyrrolate (due to decreased sweating), particularly in children and the elderly.

Diarrhea may be an early symptom of incomplete intestinal obstruction, especially in patients with ileostomy or colostomy. In this instance treatment with Glycopyrrolate Injection would be inappropriate and possibly harmful.

PRECAUTIONS

General

Investigate any tachycardia before giving Glycopyrrolate Injection since an increase in the heart rate may occur.

Use with caution in patients with: coronary artery disease; congestive heart failure; cardiac arrhythmias; hypertension; hyperthyroidism.

Use with caution in patients with renal disease since the renal elimination of glycopyrrolate may be severely impaired in patients with renal failure. Dosage adjustments may be necessary (see Pharmacokinetics - Renal Impairment).

Use glycopyrrolate with caution in the elderly and in all patients with autonomic neuropathy, hepatic disease, ulcerative colitis, prostic hypertrophy, or hiatal hernia, since anticholinergic drugs may aggravate these conditions.

The use of anticholinergetic drugs in the treatment of gastric ulcer may produce a delay in gastric emptying due to antral statis.

Information for the Patient

Because Glycopyrrolate Injection may produce drowsiness or blurred vision, the patient should be cautioned not to engage in activities requiring mental alertness and/or visual acuity such as operating a motor vehicle or other machinery, or performing hazardous work while taking this drug (see WARNINGS).

The patient also should be cautioned about the use of this drug during exercise or hot weather since overheating may result in heat stroke.

The patient may experience a possible sensitivity of the eyes to light.

Drug Interactions

The concurrent use of Glycopyrrolate Injection with other anticholinergics or medications with anticholinergic activity, such as phenothiazines, antiparkinson drugs, or tricyclic antidepressants, may intensify the antimuscarinic effects and may result in an increase in anticholinergic side effects.

Concomitant administration of Glycopyrrolate Injection and potassium chloride in a wax matrix may increase the severity of potassium chloride-induced gastrointestinal lesions as a result of a slower gastrointestinal transit time.

Carcinogenesis, Mutagenesis, Impairment of Fertility

Long-term studies in animals have not been performed to evaluate carcinogenic potential. Studies to evaluate the mutagenic potential of glycopyrrolate have not been conducted. In reproduction studies in rats, dietary administration of glycopyrrolate resulted in diminished rates of conception in a dose-related manner. Other studies in dogs suggest that this may be due to diminished seminal secretion which is evident at high doses of glycopyrrolate.

Pregnancy

TERATOGENIC EFFECTS

Reproduction studies with glycopyrrolate were performed in rats at a dietary dose of approximately 65 mg/kg/day (exposure was approximately 320 times the maximum recommended daily human dose of 2 mg on a mg/m^2 basis) and rabbits at intramuscular doses of up to 0.5 mg/kg/day (exposure was approximately 5 times the maximum recommended daily human dose on a mg/m^2 basis). These studies produced no teratogenic effects to the fetus. Because animal reproduction studies are not always predictive of human response, this drug should be used during pregnancy only if clearly needed.

Single-dose studies in humans found that very small amounts of glycopyrrolate passed the placental barrier.

NONTERATOGENIC EFFECTS

Published literature suggest the following regarding the use of glycopyrrolate during pregnancy. Unlike atropine, glycopyrrolate in normal doses (0.004 mg/kg) does not appear to affect fetal heart rate or fetal heart rate variability to a significant degree. Concentrations of glycopyrrolate in umbilical venous and aterial blood and in the amniotic fluid are low after intramuscular administration to parturients. Therefore, glycopyrrolate does not appear to penetrate through the placental barrier in significant amounts. In reproduction studies in rats, dietary administration of glycopyrrolate resulted in diminished rats of pup survival in a dose-related manner.

Nursing Mothers

It is not known whether this drug is excreted in human milk. Because many drugs are excreted in human milk, caution should be exercised when Glycopyrrolate Injection is administered to a nursing woman. As with other anticholinergics, glycopyrrolate may cause suppression of lactation (see ADVERSE REACTIONS).

Pediatric Use

Safety and effectiveness in pediatric patients have not been established for the management of peptic ulcer.

Dysrhythmias associated with the use of glycopyrrolate intravenously as a premedicant or during anesthesia have been observed in pediatric patients.

Infants, patients with Down’s syndrome, and pediatric patients with spastic paralysis or brain damage may experience an increased response to anticholinergics, thus increasing the potential for side effects.

A paradoxical reaction characterized by hyperexcitability may occur in pediatric patients taking large doses of anticholinergics including Glycopyrrolate Injection. Infants and young children are especially susceptible to the toxic effects of anticholinergics.

Geriatric Use

Clinical Studies of Glycopyrrolate Injection did not include sufficient numbers of subjects aged 65 and over to determine whether they respond differently from younger subjects. Other reported clinical experience has not identified differences in responses between the elderly and younger patients. In general, dose selection for an elderly patient should be cautious, usually starting at the low end of the dosing range, reflecting the greater frequency of decreased hepatic, renal, or cardiac function, and of concomitant disease or other therapy.

ADVERSE REACTIONS

Anticholinergics, including Glycopyrrolate Injection, can produce certain effects, most of which are extensions of their pharmacologic actions. Adverse reactions may include xerostomia (dry mouth); urinary hesitancy and retention; blurred vision and photophobia due to mydriasis (dilation of the pupil); cycloplegia; increased ocular tension; tachycardia; palpitation; decreased sweating; loss of taste; headache; nervousness; drowsiness; weakness; dizziness; insomnia; nausea; vomiting; impotence; suppression of lactation; constipation; bloated feeling; severe allergic reactions including anaphylactic/anaphylactoid reactions; hypersensitivity; urticaria, pruritus, dry skin, and other dermal manifestations; some degree of mental confusion and/or excitement, especially in elderly persons.

In addition, the following adverse events have been reported from post-marketing experience with glycopyrrolate: malignant hyperthermia; cardiac arrhythmias (including bradycardia, ventricular tachycardia, ventricular fibrillation); cardiac arrest; hypertension; hypotension; seizures; and respiratory arrest. Post-marketing reports have included cases of heart block and QTc interval prolongation associated with the combined use of glycopyrrolate and an anticholinesterase. Injection site reactions including pruritus, edema, erythema, and pain have also been reported.

Glycopyrrolate is chemically a quaternary ammonium compound; hence, its passage across lipid membranes, such as the blood-brain barrier is limited in contrast to atropine sulfate and scopolamine hydrobromide. For this reason the occurrence of CNS-related side effects is lower, in comparison to their incidence following administration of anticholinergics which are chemically tertiary amines that can cross this barrier readily.

OVERDOSAGE

To combat peripheral anticholinergic effects, a quaternary ammonium anticholinesterase such as neostigmine methylsulfate (which does not cross the blood-brain barrier) may be given intravenously in increments of 0.25 mg in adults. This dosage may be repeated every five to ten minutes until anticholinergic overactivity is reversed or up to a maximum of 2.5 mg. Proportionately smaller doses should be used in pediatric patients. Indication for repetitive doses of neostigmine should be based on close monitoring of the decrease in heart rate and the return of bowel sounds.

If CNS symptoms (e.g., excitement, restlessness, convulsions, psychotic behavior) occur, physostigmine (which does cross the blood–brain barrier) may be used. Physostigmine 0.5 to 2 mg should be slowly administered intravenously and repeated as necessary up to a total of 5 mg in adults. Proportionately smaller doses should be used in pediatric patients.

To combat hypotension, administer IV fluids and/or pressor agents along with supportive care.

Fever should be treated symptomatically.

Following overdosage, a curare-like action may occur, i.e., neuromuscular blockade leading to muscular weakness and possible paralysis. In the event of a curare-like effect on respiratory muscles, artificial respiration should be instituted and maintained until effective respiratory action returns.

DOSAGE AND ADMINISTRATION

Parenteral drug products should be inspected visually for particulate matter and discoloration prior to administration whenever solution and container permit.

Glycopyrrolate Injection may be administered intramuscularly, or intravenously, without dilution, in the following indications.

Adults

PREANESTHETIC MEDICATION

The recommended dose of Glycopyrrolate Injection is 0.004 mg/kg by intramuscular injection, given 30 to 60 minutes prior to the anticipated time of induction of anesthesia or at the time the preanesthetic narcotic and/or sedative are administered.

INTRAOPERATIVE MEDICATION

Glycopyrrolate Injection may be used during surgery to counteract drug-induced or vagal reflexes and their associated arrhythmias (e.g., bradycardia). It should be administered intravenously as single doses of 0.1 mg and repeated, as needed, at intervals of 2 to 3 minutes. The usual attempts should be made to determine the etiology of the arrhythmia, and the surgical or anesthetic manipulations necessary to correct parasympathetic imbalance should be performed.

REVERSAL OF NEUROMUSCULAR BLOCKADE

The recommended dose of Glycopyrrolate Injection is 0.2 mg for each 1 mg of neostigmine or 5 mg of pyridostigmine. In order to minimize the appearance of cardiac side effects, the drugs may be administered simultaneously by intravenous injection and may be mixed in the same syringe.

PEPTIC ULCER

The usual recommended dose of Glycopyrrolate Injection is 0.1 mg administered at 4-hour intervals, 3 or 4 times daily intravenously or intramuscularly. Where more profound effect is required, 0.2 mg may be given. Some patients may need only a single dose, and frequency of administration should be dictated by patient response up to a maximum of four times daily.

Glycopyrrolate Injection is not recommended for the treatment of peptic ulcer in pediatric patients (see PRECAUTIONS – Pediatric Use).

Pediatric Patients

(see PRECAUTIONS - Pediatric Use)

PREANESTHETIC MEDICATION

The recommended dose of Glycopyrrolate Injection in pediatric patients is 0.004 mg/kg intramuscularly, given 30 to 60 minutes prior to the anticipated time of induction of anesthesia or at the time the preanesthetic narcotic and/or sedative are administered.

Do not use this prefilled syringe to administer a dose of less than 0.1 mg (0.5 mL).

INFANTS

(1 month to 2 years of age) may require up to 0.009 mg/kg.

Do not use this prefilled syringe to administer a dose of less than 0.1 mg (0.5 mL).

INTRAOPERATIVE MEDICATION

Because of the long duration of action of Glycopyrrolate Injection if used as preanesthetic medication, additional Glycopyrrolate Injection for anticholinergic effect intraoperatively is rarely needed; in the event it is required the recommended pediatric dose is 0.004 mg/kg intravenously, not to exceed 0.1 mg in a single dose which may be repeated, as needed, at intervals of 2 to 3 minutes. The usual attempts should be made to determine the etiology of the arrhythmia, and the surgical or anesthetic manipulations necessary to correct parasympathetic imbalance should be performed.

Do not use this prefilled syringe to administer a dose of less than 0.1 mg (0.5 mL).

REVERSAL OF NEUROMUSCULAR BLOCKADE

The recommended pediatric dose of Glycopyrrolate Injection is 0.2 mg for each 1 mg of neostigmine or 5 mg of pyridostigmine. In order to minimize the appearance of cardiac side effects, the drugs may be administered simultaneously by intravenous injection and may be mixed in the same syringe.

Do not use this prefilled syringe to administer a dose of less than 0.1 mg (0.5 mL).

PEPTIC ULCER

Glycopyrrolate Injection is not recommended for the treatment of peptic ulcer in pediatric patients (see PRECAUTIONS – Pediatric Use).

Diluent Compatibilities

Dextrose 5% and 10% in water, or saline, dextrose 5% in sodium chloride 0.45%, sodium chloride 0.9%, and Ringer’s Injection.

Diluent Incompatibilities

Lactated Ringer’s solution

Admixture Compatibilities

PHYSICAL COMPATIBILITY

This list does not constitute an endorsement of the clinical utility or safety of co-administration of glycopyrrolate with these drugs. Glycopyrrolate Injection is compatible for mixing and injection with the following injectable dosage forms: atropine sulfate, USP; Antilirium® (physostigmine salicylate); Benadryl® (diphenhydramine HCl); codeine phosphate, USP; Emete-Con® (benz-quinamide HCl); hydromorphone HCl, USP; Inapsine® (droperidol); Levo-Dromoran® (levorphanol tartrate); lidocaine, USP; meperidine HCl, USP; Mestinon® /Regonol® (pyridostigmine bromide); morphine sulfate, USP; Nubain® (nalbuphine HCl); Numorphan® (oxymorphone HCl); procaine HCl, USP; promethazine HCl, USP; Prostigmin® (neostigmine methylsulfate, USP); scopolamine HBr, USP; Stadol® (butorphanol tartrate); Sublimaze® (fentanyl citrate); Tigan® (trimethobenzamide HCl); and Vistaril® (hydroxyzine HCl). Glycopyrrolate Injection may be administered via the tubing of a running infusion of normal saline.

Admixture Incompatibilities

PHYSICAL INCOMPATIBILITY

Since the stability of glycopyrrolate is questionable above a pH of 6.0 do not combine Glycopyrrolate Injection in the same syringe with Brevital® (methohexital Na); Chloromycetin® (chloramphenicol Na succinate); Dramamine® (dimenhydrinate); Nembutal® (pentobarbital Na); Pentothal® (thiopental Na); Seconal® (secobarbital Na); sodium bicarbonate (Abbott); Valium® (diazepam); Decadron® (dexamethasone Na phosphate); or Talwin® (pentazocine lactate). These mixtures will result in a pH higher than 6.0 and may result in gas production or precipitation.

HOW SUPPLIED

Glycopyrrolate Injection, USP, 0.2 mg per mL is available as a preservative-free, clear, colorless solution supplied in single-dose prefilled syringes as follows:

1 mL single-dose prefilled disposable syringe packaged in 10s (NDC 0641-6212-10)

2 mL single-dose prefilled disposable syringe packaged in 10s (NDC 0641-6213-10)

Store at 20°C to 25°C (68°F to 77°F) [see USP Controlled Room Temperature].

Discard unused portion.

Sensitive to heat – Do not autoclave.

Do not place syringe on a sterile field.

To report SUSPECTED ADVERSE REACTIONS, contact Hikma Pharmaceuticals USA Inc. at 1-877-845-0689, or the FDA at 1-800-FDA-1088 or www.fda.gov/medwatch.

For Product Inquiry call 1-877-845-0689.

INSTRUCTIONS FOR USE

CAUTION: Glass syringes may malfunction, break or clog when connected to some Needleless Luer Access Devices (NLADs) and needles. The external collar must remain attached to the syringe (See Figure 1). Spontaneous disconnection of this glass syringe from needles and NLADs with leakage of drug product may occur. Assure that the needle or NLAD is securely attached before beginning the injection. Inspect the glass syringe-needle or glass syringe –NLAD connection before and during drug administration.

Figure 1

Syringe Image

Glycopyrrolate Injection may be administered intramuscularly or intravenously. Parenteral drug products should be inspected visually for particulate matter and discoloration prior to administration whenever solution and container permit.

1. Inspect the outer packaging (plastic tube) and the syringe label by verifying:

- plastic tube integrity

- drug name

- drug strength

- fill volume

- route of administration

- expiration date to be sure that the drug has not expired

- sterile field applicability

Do not use if package has been damaged.

2. Open the outer packaging and remove the syringe from the tube.

3. Perform visual inspection on the syringe by verifying:

- absence of syringe damage

- absence of external particles

- absence of internal particles

- proper drug color

4.Push plunger rod slightly to break the stopper loose while tip cap is still on.

5. Remove tip cap by twisting it off. (See Figure 2)

Figure 2

Figure 2

6. Discard the tip cap.

7. Expel air bubble.

8. Adjust dose into sterile material (if applicable).

9. Connect the syringe to appropriate injection connection depending on route of administration.

-Before injection, ensure that the syringe is securely attached to the needle or NLAD.

10. Depress plunger rod to deliver the required dose of medication. Ensure that pressure is maintained on the plunger rod during the entire administration.

11. Remove the syringe from NLAD (if applicable) and discard into appropriate receptacle.

When a needle is connected to the syringe, to prevent needle-stick injuries, do not recap needles.

NOTES:

- All steps must be performed sequentially
- Do not autoclave syringe
- Do not use this product on a sterile field
- Do not introduce any other fluid into the syringe at any time
- This product is for single dose only; discard unused portion

Manufactured by:

Hikma Pharmaceuticals USA Inc.

Berkeley Heights, NJ 07922

462-059-01

Revised July 2025

PRINCIPAL DISPLAY PANEL

NDC 0641-6212-01Rx only

1 mL Single-Dose Prefilled Syringe

Glycopyrrolate Injection, USP
0.2 mg/mL
For IM or IV Use

Preservative-Free. Discard unused portion.

NDC 0641-6212-10 Rx only

Glycopyrrolate Injection, USP
0.2 mg/mL
For Intramuscular or Intravenous Use

Preservative-Free.

10 x 1 mL Single-Dose Prefilled Syringes

Discard unused portion.

PRINCIPAL DISPLAY PANEL

NDC 0641-6213-01Rx only

2 mL Single-Dose Prefilled Syringe

Glycopyrrolate Injection, USP
0.4 mg per 2 mL (0.2 mg/mL)
For IM or IV Use. Preservative-Free. Discard unused portion.

NDC 0641-6213-10 Rx only

Glycopyrrolate Injection, USP
0.4 mg per 2 mL (0.2 mg/mL)
For Intramuscular or Intravenous Use

Preservative-Free.

10 x 2 mL Single-Dose Prefilled Syringes

Discard unused portion.